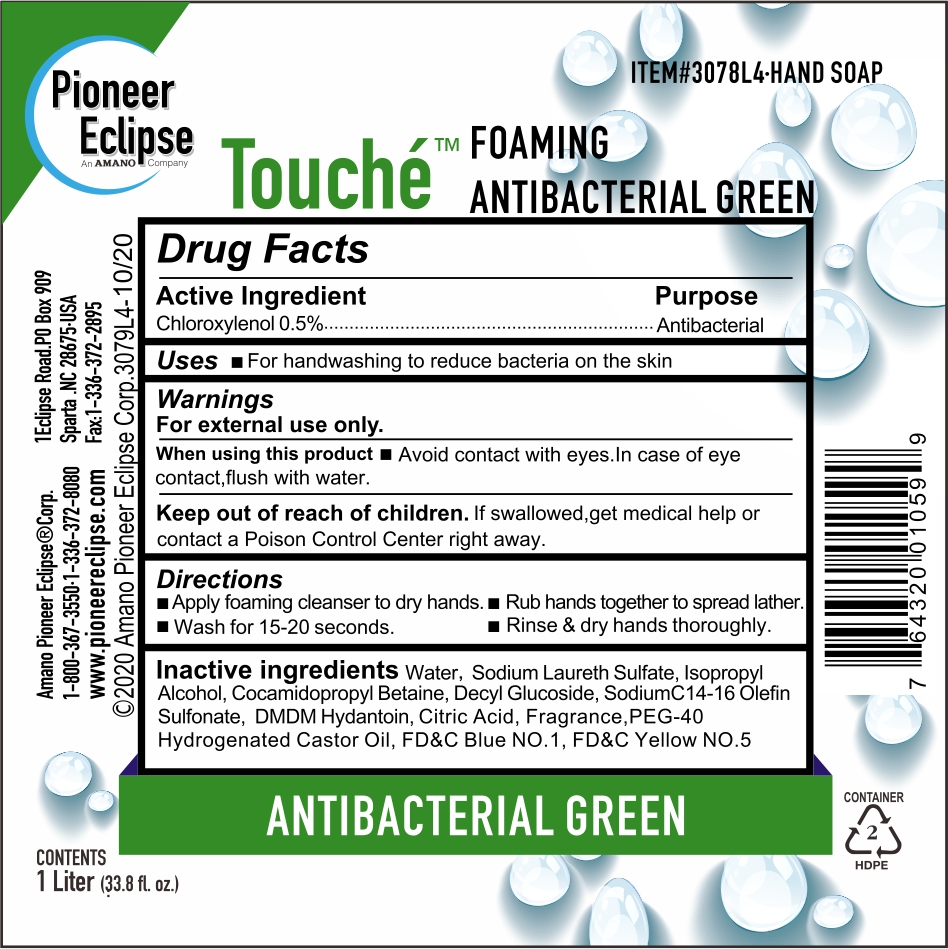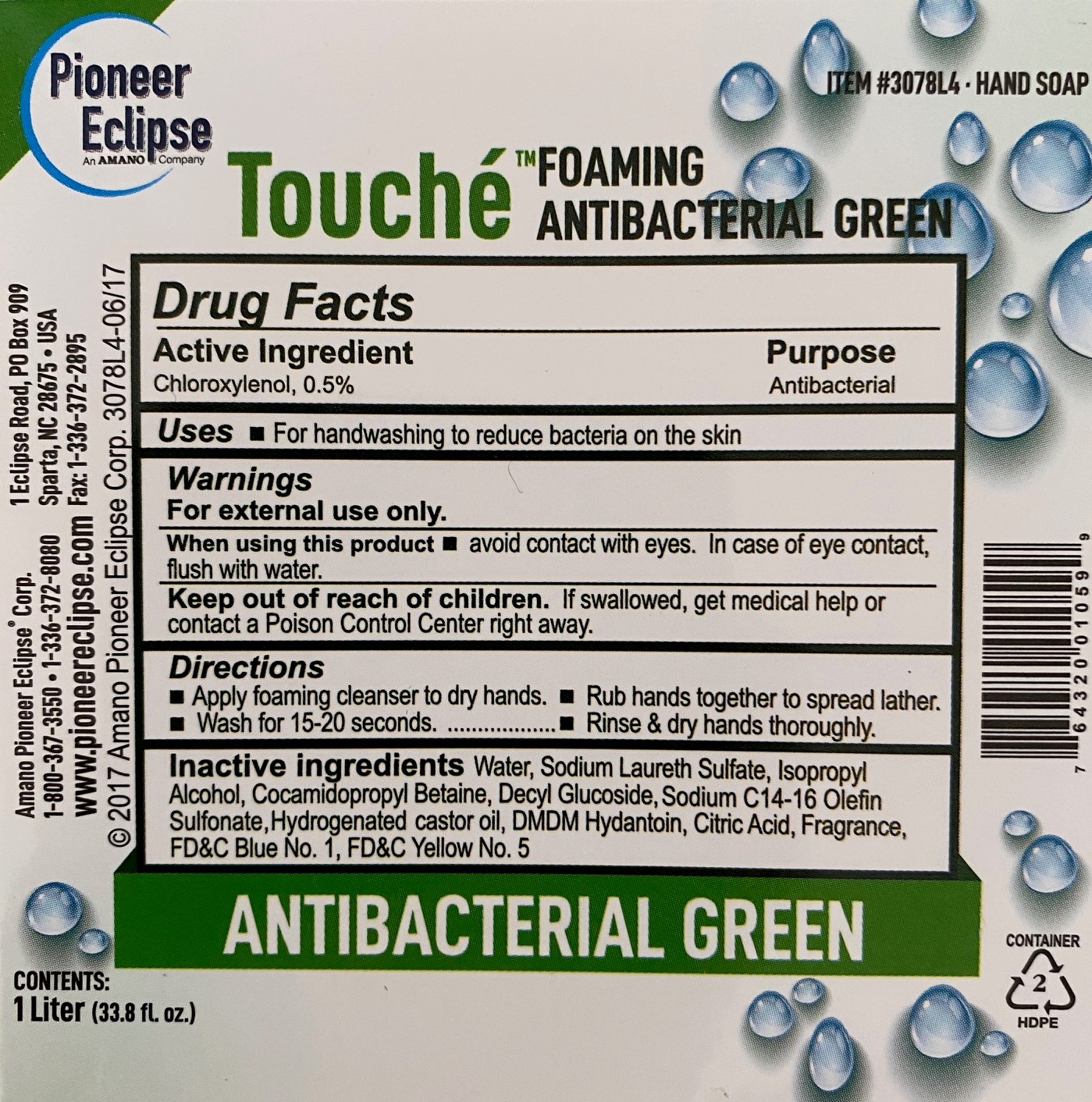 DRUG LABEL: Foaming Antibacterial Green
NDC: 80401-110 | Form: LIQUID
Manufacturer: Uweport LLC
Category: otc | Type: HUMAN OTC DRUG LABEL
Date: 20211230

ACTIVE INGREDIENTS: CHLOROXYLENOL 0.5 g/100 mL
INACTIVE INGREDIENTS: SODIUM C14-16 OLEFIN SULFONATE 2 mL/100 mL; SODIUM LAURETH SULFATE 6 mL/100 mL; WATER; ISOPROPYL ALCOHOL 3 mL/100 mL; COCAMIDOPROPYL BETAINE 2 mL/100 mL; DECYL GLUCOSIDE 1 mL/100 mL; CHLOROCITRIC ACID 0.015 mL/100 mL; POLYOXYL 40 HYDROGENATED CASTOR OIL 0.2 mL/100 mL; DMDM HYDANTOIN 0.3 mL/100 mL

The hand sanitizer is manufactured using only the following United States Pharmacopoeia (USP) grade ingredients in the preparation of the product (percentage in final product formulation) consistent with World Health Organization (WHO) recommendations:

1. Isopropyl Alcohol (3%, v/v) in an aqueous solution denatured according to Alcohol and Tobacco Tax and Trade Bureau regulations in 27 CFR part 20.
2. Chloroxylenol (0.5% w/v).
3. Sodium Laureth Sulfate (6% v/v).
4. Cocamidopropyl Betaine (2% v/v).
5. Decyl Glucoside (1% v/v)
6. Sodium C14-16 Olefin Sulfonate (2% v/v)
7. DMDM Hydantoin (0.3% v/v)
8. Citric Acid (0.015% v/v)
9. PEG-40 Hydrogenated castor oil (0.2% v/v)
10. Sterile distilled water or boiled cold water.

The firm does not add other active or inactive ingredients. Different or additional ingredients may impact the quality and potency of the product.

Active Ingredient(s)

Chloroxylenol 0.5% w/v. Purpose: Antiseptic

Purpose

Antiseptic, Hand Sanitizer

Use

Hand Sanitizer to help reduce bacteria that potentially can cause disease. For use when soap and water are not available.

Warnings

For external use only. Flammable. Keep away from heat or flame

Do not use

- in children less than 2 months of age
- on open skin wounds

When using this product keep out of eyes, ears, and mouth. In case of contact with eyes, rinse eyes thoroughly with water.
Stop use and ask a doctor if irritation or rash occurs. These may be signs of a serious condition.
Keep out of reach of children. If swallowed, get medical help or contact a Poison Control Center right away.

Stop use and ask a doctor if irritation or rash occurs. These may be signs of a serious condition.

Keep out of reach of children. If swallowed, get medical help or contact a Poison Control Center right away.

Directions

- Place enough product on hands to cover all surfaces. Rub hands together until dry.
- Supervise children under 6 years of age when using this product to avoid swallowing.

Other information

- Store between 15-30C (59-86F)
- Avoid freezing and excessive heat above 40C (104F)

Inactive ingredients

Sodium Laureth Sulfate, Isopropyl Alcohol, Cocamidopropyl Betaine, Decyl Glucoside, Sodium C14-16 Olefin Sulfonate, DMDM Hydantoin, Citric Acid, PEG-40 Hydrogenated castor oil, FD&C Blue NO.1, FD&C Yellow NO.5,purified water USP

Package Label - Principal Display Panel

1000 ml NDC: 80401-110-10